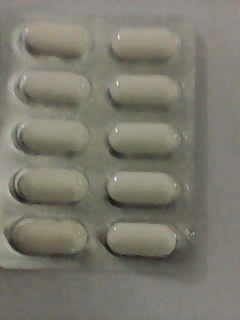 DRUG LABEL: APCAL
NDC: 46084-071 | Form: TABLET
Manufacturer: A P J Laboratories limited
Category: otc | Type: HUMAN OTC DRUG LABEL
Date: 20130221

ACTIVE INGREDIENTS: CALCIUM CARBONATE 1250 mg/1 1; CHOLECALCIFEROL 250 [iU]/1 1
INACTIVE INGREDIENTS: STARCH, CORN 20 mg/1 1; GELATIN 2 mg/1 1; METHYLPARABEN 2 mg/1 1; TITANIUM DIOXIDE .1 mg/1 1; MAGNESIUM STEARATE 20 mg/1 1; TALC 20 mg/1 1; SODIUM STARCH GLYCOLATE TYPE A POTATO 10 mg/1 1; SILICON DIOXIDE 10 1/1 1

Ask a doctor or pharmacist before use if you are taking a prescription drug.

INACTIVE INGREDIENT

STARCH, CORN

INACTIVE INGREDIENT

GELATIN

INACTIVE INGREDIENT

METHYLPARABEN

INACTIVE INGREDIENT

TITANIUM DIOXIDE

INACTIVE INGREDIENT

TALC

INACTIVE INGREDIENT

SODIUM STARCH GLYCOLATE TYPE A POTATO

INACTIVE INGREDIENT

SILICON DIOXIDE

Keep out of reach of children.

PURPOSE

Supplement

INDICATIONS AND USAGE

Enter section text here

PACKAGE LABEL

product

ACTIVE INGREDIENT

Enter section text here

DOSAGE AND ADMINISTRATION

Calcium Carbonate 1250 mg Vitamin D3 250 IU